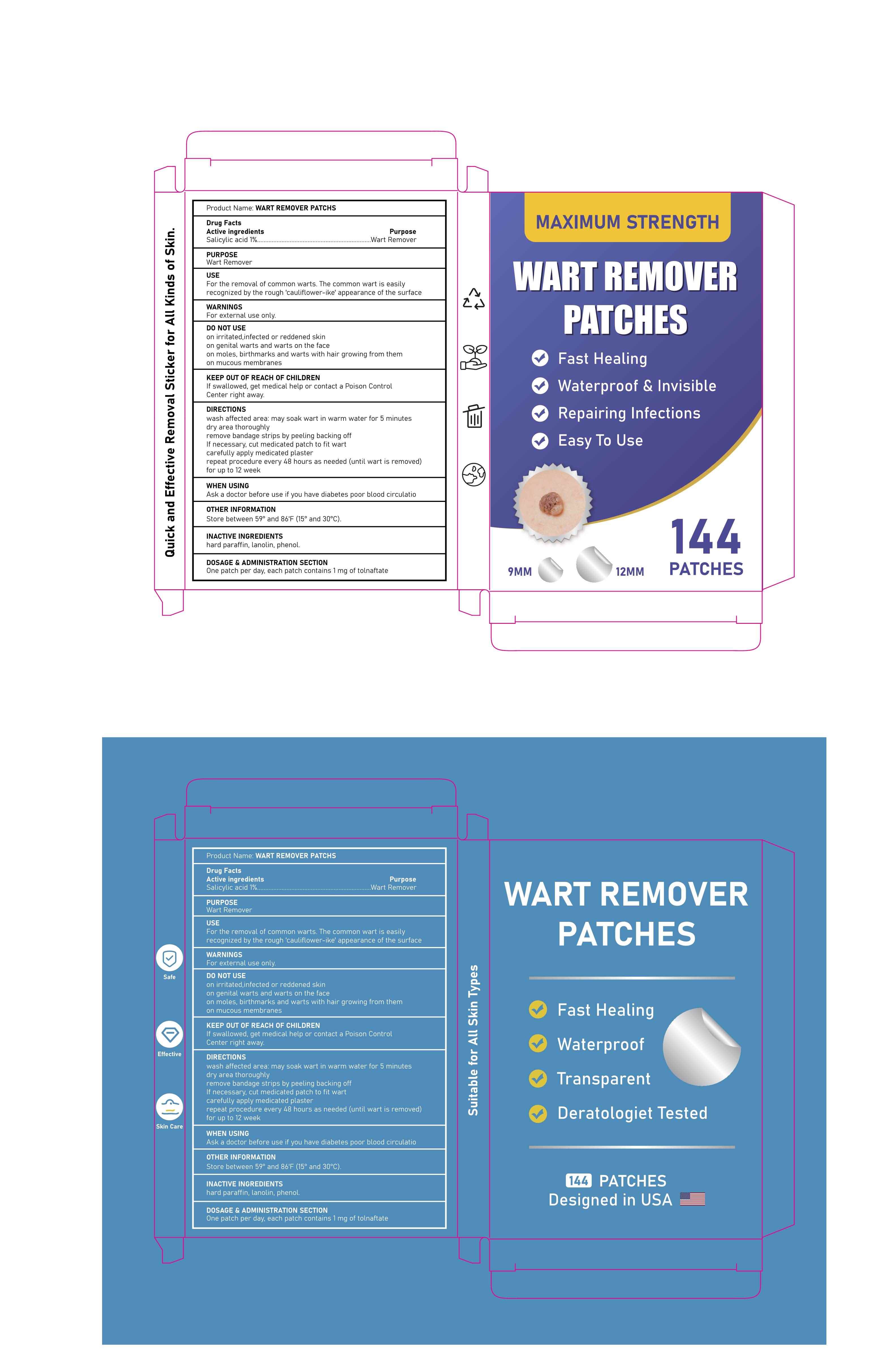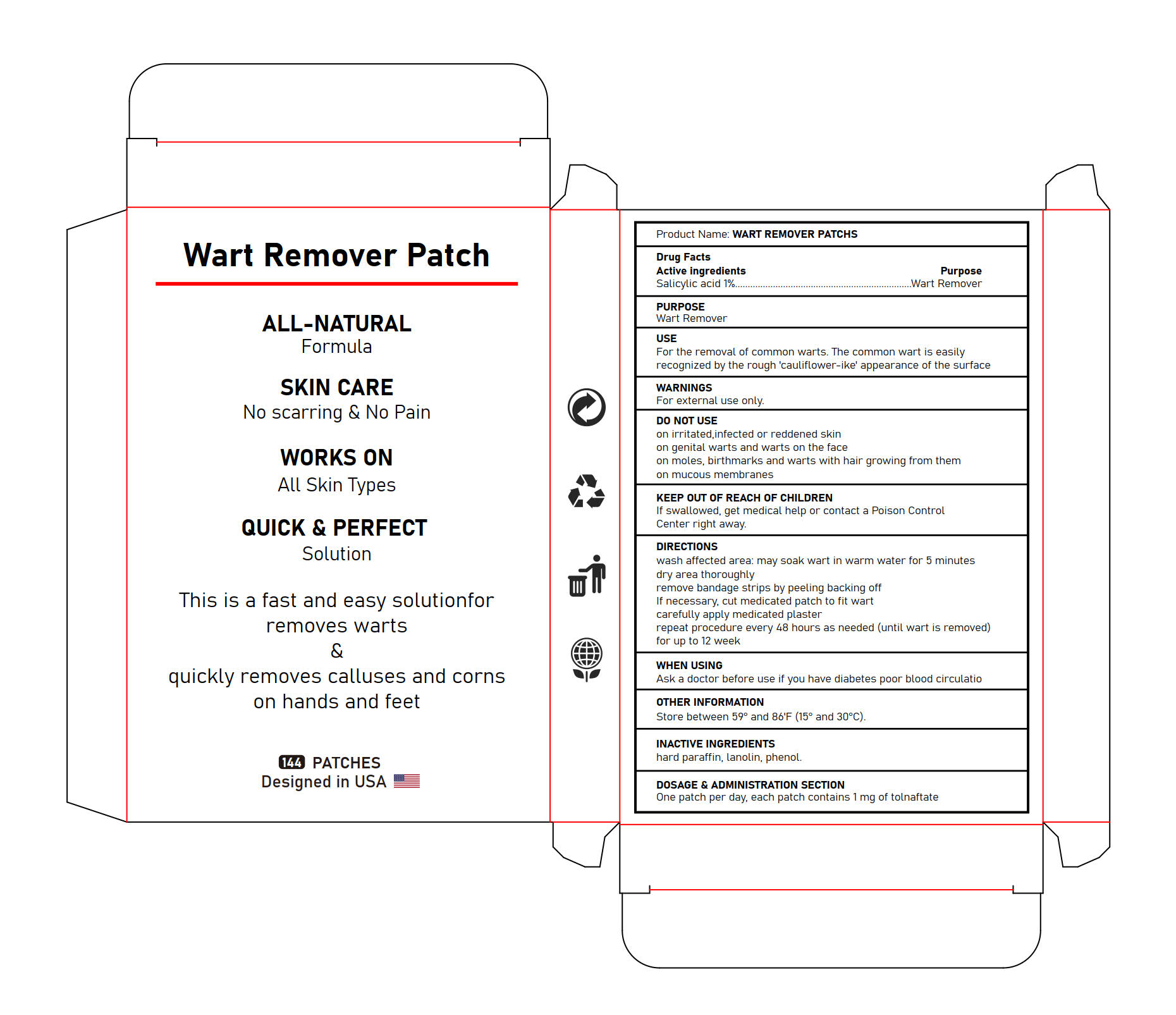 DRUG LABEL: Wart Remover Patch
NDC: 84023-110 | Form: PATCH
Manufacturer: Shenzhen Yangan Technology Co., Ltd.
Category: otc | Type: HUMAN OTC DRUG LABEL
Date: 20240927

ACTIVE INGREDIENTS: SALICYLIC ACID 1 mg/100 mg
INACTIVE INGREDIENTS: LANOLIN; PARAFFIN; PHENOL

ACTIVE INGREDIENT

salicylic acid 1%

PURPOSE

Wart Remover

WARNINGS

For external use only.

DO NOT USE

on irritated, infected or reddened skin

on genital warts and warts on the face

on moles, birthmarks and warts with hair growing form them

on mucous membranes

keep out of reach of children

If swallowed, get medica help or contact a Poison Control Center right way

when using

Ask a doctor before use if you have diabetes poor blood circulatio

DOSAGE AND ADMINISTRATION

One patch per day, each patch contains 1 mg of tolnaftate.

OTHER SAFETY INFORMATION

Store between 59° and 86'F (15° and 30° C)

INACTIVE INGREDIENT

hard paraffin, lanolin, phenol

DIRECTIONS

wash affected area:may soak wart in warm water for 5 minutes

dry area thoroughly

remove bandage strips by peeling backing off

if necessary, cut medicated patch to fit wart

carefully apply medicated plaster

repeat procedure every 48 hours as needed(until wart is removed)

for up to 12 week